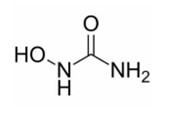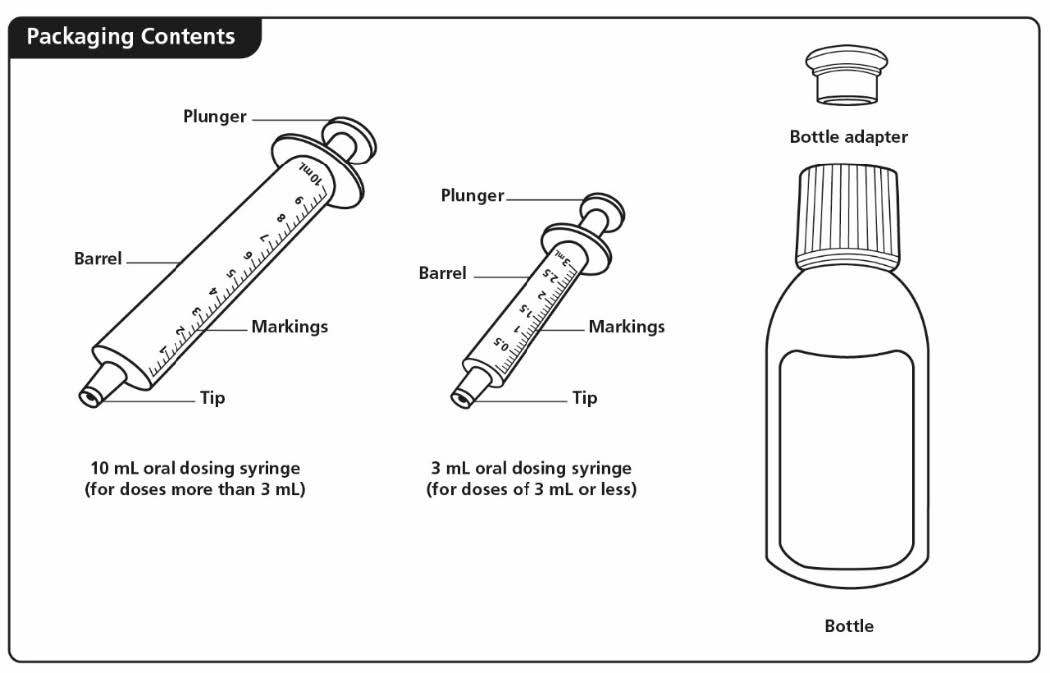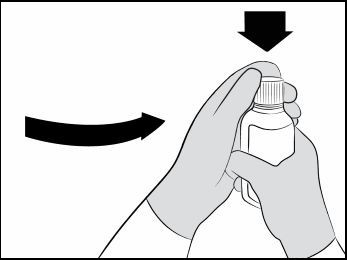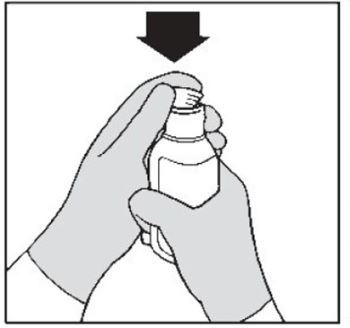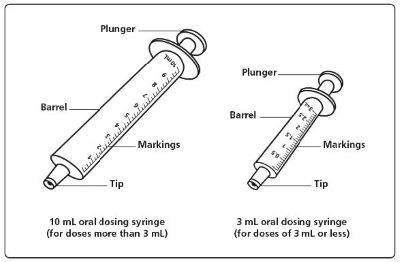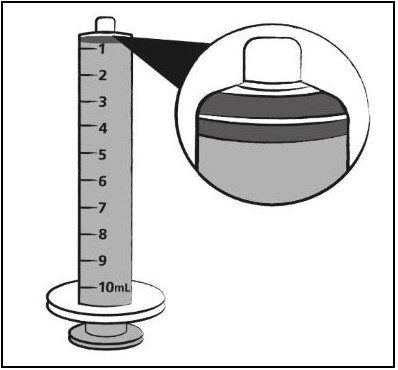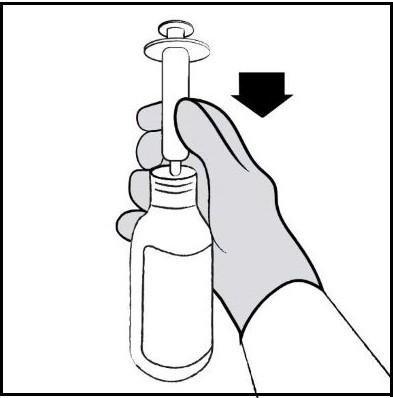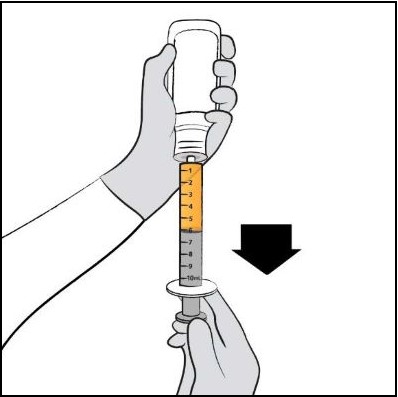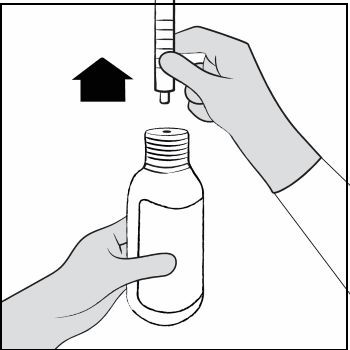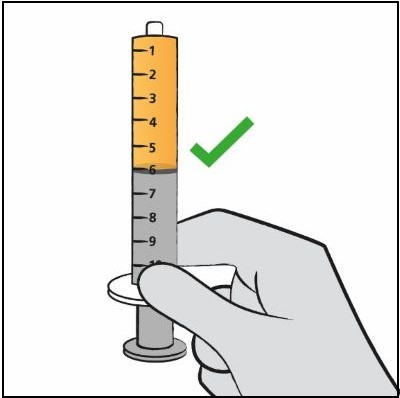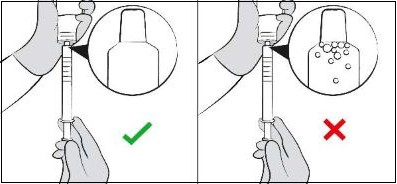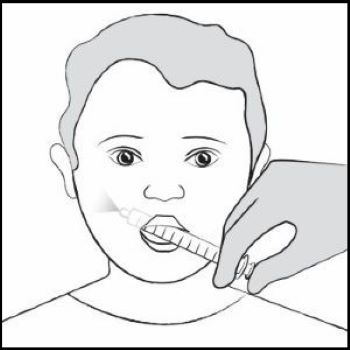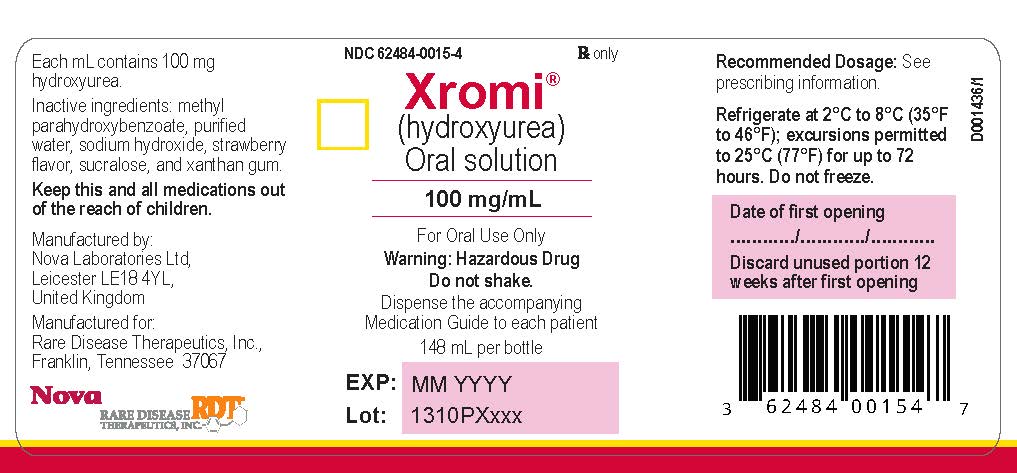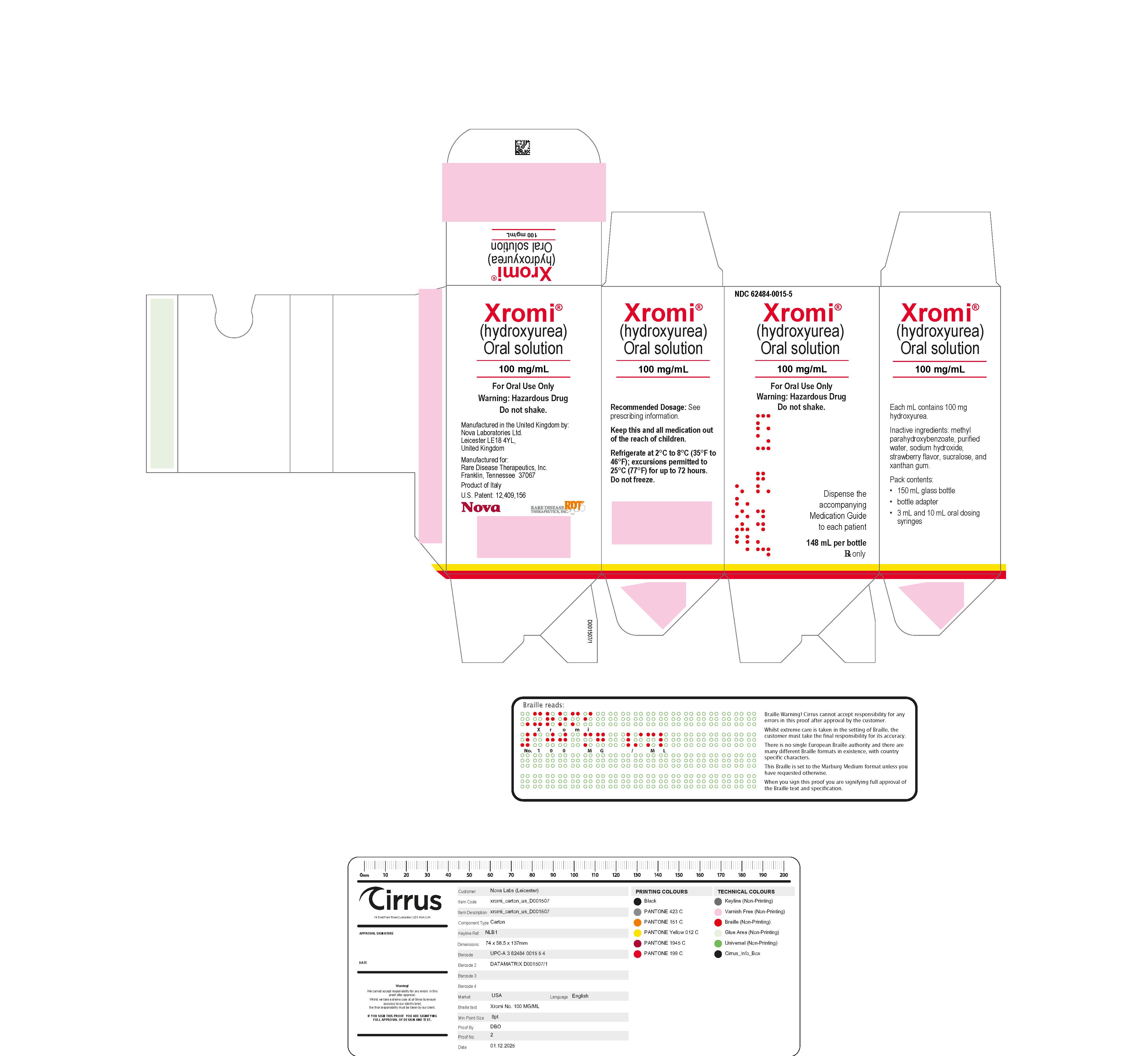 DRUG LABEL: XROMI
NDC: 62484-0015 | Form: SOLUTION
Manufacturer: Nova Laboratories, Ltd.
Category: prescription | Type: HUMAN PRESCRIPTION DRUG LABEL
Date: 20260202

ACTIVE INGREDIENTS: Hydroxyurea 100 mg/1 mL

HIGHLIGHTS OF PRESCRIBING INFORMATION

These highlights do not include all the information needed to use XROMI safely and effectively. See full prescribing information for XROMI.
XROMI (hydroxyurea) oral solution
Initial U.S. Approval: 1967

WARNING: MYELOSUPPRESSION and MALIGNANCIES

See full prescribing information for complete boxed warning.

- Myelosuppression:XROMI may cause severe myelosuppression. Do not give if bone marrow function is markedly depressed. Monitor blood counts at baseline and throughout treatment. Interrupt treatment and reduce dose as necessary (5.1).
- Malignancies Hydroxyurea is carcinogenic. Advise sun protection and monitor patients for malignancies (5.3).

1 INDICATIONS AND USAGE

- XROMI is an antimetabolite indicated to reduce the frequency of painful crises and reduce the need for blood transfusions in pediatric patients aged 6 months of age and older with sickle cell anemia with recurrent moderate to severe painful crises. (1)

2 DOSAGE AND ADMINISTRATION

- Initial dose: 15 mg/kg orally once daily. Monitor the patient’s blood count every two weeks. (2.1)
- The dose may be increased by 5 mg/kg/day every 8 to 12 weeks until a maximum tolerated dose or 35 mg/kg/day is reached if blood counts are in an acceptable range. (2.1)
- The dose is not increased if blood counts are below the acceptable range and toxic. Discontinue XROMI until hematologic recovery if blood counts are considered toxic. Treatment may be resumed after reducing the dose by 2.5mg/kg/day to 5mg/kg/day from the dose associated with hematological toxicity. (2.1)
- Renal impairment: Reduce the dose of XROMI by 50% in patients with creatinine clearance less than 60 mL/min. (2.2, 8.6, 12.3)

3 DOSAGE FORMS AND STRENGTHS

- Oral Solution: 100 mg/mL in a 148 mL multiple-dose bottle (3)

4 CONTRAINDICATIONS

- In patients who have demonstrated a previous hypersensitivity to hydroxyurea or any other component of its formulation. (4)

5 WARNINGS AND PRECAUTIONS

- Hemolytic anemia: Monitor blood counts throughout treatment. If hemolysis persists, discontinue XROMI. (5.2)
- Embryo-Fetal toxicity: Can cause fetal harm. Advise of potential risk to a fetus and use of effective contraception. (5.4, 8.1, 8.3)
- Vasculitic toxicities: Institute treatment and discontinue XROMI if this occurs. (5.5)
- Live Vaccinations: Avoid live vaccine use in a patient taking XROMI. (5.6)
- Risks with concomitant use of antiretroviral drugs: Pancreatitis, hepatotoxicity, and neuropathy have occurred. Monitor for signs and symptoms in patients with HIV infection using antiretroviral drugs; discontinue XROMI and implement treatment. (5.7)

6 ADVERSE REACTIONS

Most common adverse reactions (incidence > 5%) are neutropenia and thrombocytopenia, and popular rash. (6)
To report SUSPECTED ADVERSE REACTIONS, contact Rare Disease Therapeutics, Inc. at 844-472-7389
or FDA at 1-800-FDA-1088 or www.fda.gov/medwatch.

7 DRUG INTERACTIONS

- Antiretroviral drug. (7.1)
- Laboratory Test Interference. (7.2)

FULL PRESCRIBING INFORMATION

WARNING: MYELOSUPPRESSION and MALIGNANCIES

- Myelosuppression: XROMI may cause severe myelosuppression. Do not give if bone marrow function is markedly depressed. Monitor blood counts at baseline and throughout treatment. Interrupt treatment and reduce dose as necessary [see Warnings and Precautions(5.1)].
- Malignancies: Hydroxyurea is carcinogenic. Advise sun protection and monitor patients for malignancies [see Warnings and Precautions (5.3)].

1 INDICATIONS AND USAGE

XROMI is indicated to reduce the frequency of painful crises and reduce the need for blood transfusions in pediatric patients aged 6 months of age and older with sickle cell anemia with recurrent moderate to severe painful crises.

2 DOSAGE AND ADMINISTRATION

2.1 Recommended Dosage

The recommended XROMI dosage in pediatric patients aged 6 months and older is described in Table 1.

Table 1. Dosing Recommendation Based on Blood Count
Dosing Regimen | Dose | Dose modification criteria | Monitoring parameters
Initial Recommended dosing | 15 mg/kg/day (rounded to nearest 10 mg) orally as a single dose once daily based on the patient’s actual body weight. |  | Monitor the patient’s complete blood count (CBC) with differential and reticulocyte count every 2 weeks while adjusting dosage [see Warnings and Precautions (5.1)].
Dosing Adjustment Based on Blood Counts in the acceptable range | Increase dose 5 mg/kg/day every 8 to 12 weeks. Maximal dose: 35 mg/kg/day.* *Maximal dose is the highest dose that does not produce toxic blood counts over 24 consecutive weeks. | Increase dose only if blood counts are in an acceptable range. Do not increase if myelosuppression occurs. | Target Blood Counts Absolute neutrophil count (ANC) 1 to 3 x 10^9/L and platelets at least 80 x 10^9/L
Dosing Adjustment Based on Blood Counts below acceptable range | Do not increase dose. | If blood counts are considered toxic, discontinue XROMI until hematologic recovery. | Blood Counts Toxic Range; - ANC less than 1 x 10^9/L - Platelets less than 80 x 10^9/L - Hemoglobin 20% decrease from baseline or hemoglobin less than 4.5 g/dL - Reticulocytes less than 80 x 10^9/L if the hemoglobin concentration is less than 9 g/dL.
Dosing after Hematologic Recovery | If hematologic toxicity resolved within 1 week, restart at the same XROMI dose. If hematologic toxicity persisted for more than 1 week or occurred twice in a 3 month period, reduce dose by 5 mg/kg/day. |  | Once a stable dose is established, monitor CBC with differential and reticulocyte count every 4 weeks for 2 months and then as clinically indicated.

Caregivers must be able to follow directions regarding drug administration and their monitoring and care.

If a dose of XROMI is missed at the scheduled time, the patient should take the missed dose as soon as possible once it is noticed, but only on the same day. If this is not possible, the patient should skip the dose and continue with the next dose as prescribed.

The patient should not take two doses to make up for a missed dose.

Fetal hemoglobin (HbF) levels may be used to evaluate the efficacy of XROMI in clinical use. Obtain HbF levels every three to four months. Monitor for an increase in HbF of at least two-fold over the baseline value.

XROMI causes macrocytosis, which may mask the incidental development of folic acid deficiency. Prophylactic administration of folic acid is recommended.

2.2 Administration Instructions

XROMI is for oral use. See Instructions for Use for details on preparation and administration of XROMI for oral solution.
Do not shake.
Two oral dosing syringes (one oral dosing syringe graduated to 3 mL and one oral dosing syringe graduated to 10 mL) are provided for accurate measurement of the prescribed dose of the oral solution. It is recommended that the healthcare professional advises the caregiver which oral dosing syringe to use to ensure that the correct volume is administered.
The smaller 3 mL oral dosing syringe, marked from 0.5 mL to 3 mL, is for measuring doses of less than or equal to 3 mL. This oral dosing syringe should be recommended for doses less than or equal to 3 mL (each graduation of 0.1 mL contains 10 mg of hydroxyurea).
The larger 10 mL oral dosing syringe, marked 1 mL to 10 mL, is for measuring doses of more than 3 mL. This oral dosing syringe should be recommended for doses greater than 3 mL (each graduation of 0.25 mL contains 25 mg of hydroxyurea).
XROMI may be taken with or after meals at any time of the day but caregivers should standardize the method of administration and time of day.
XROMI is a hazardous drug. Follow applicable special handling and disposal procedures [see Reference (15)].

2.3 Dosage Modifications in Renal Impairment

Reduce the dose of XROMI by 50% in patients with creatinine clearance of less than 60 mL/min or with end-stage renal disease (ESRD) [see Use in Specific Populations (8.6) and Clinical Pharmacology (12.3)]. Creatinine clearance were obtained using 24-hour urine collection.

Table 2. Creatinine Clearance
Creatinine Clearance (mL/min) | Recommended XROMI Initial Dose
Greater than or equal to 60 | 15 mg/kg once daily
Less than 60 or ESRD* | 7.5 mg/kg once daily
* On dialysis days, administer XROMI to patients with ESRD following hemodialysis

Monitor the hematologic parameters closely in these patients.

3 DOSAGE FORMS AND STRENGTHS

Oral solution: 100 mg/mL clear colorless to pale yellow liquid in a multiple-dose amber bottle.

4 CONTRAINDICATIONS

XROMI is contraindicated in patients:

- who have demonstrated a previous hypersensitivity to hydroxyurea or any other component of its formulation. [see Adverse Reactions (6)].

5 WARNINGS AND PRECAUTIONS

5.1 Myelosuppression

Hydroxyurea causes severe myelosuppression. Do not initiate treatment with XROMI in patients if bone marrow function is markedly depressed. Bone marrow suppression may occur, and leukopenia is generally its first and most common manifestation. Thrombocytopenia and anemia occur less often and are seldom seen without a preceding leukopenia.

Some patients, treated at the recommended initial dose of 15 mg/kg/day, have experienced severe or life-threatening myelosuppression.

Evaluate hematologic status (CBC, reticulocyte count) prior to and every 2 weeks during dose-escalation period of XROMI treatment. Once a stable dose of XROMI is achieved, monitor every 4 weeks. Provide supportive care and modify dose or discontinue XROMI as needed. Recovery from myelosuppression is usually rapid when therapy is interrupted. [see Dosage and Administration (2.1)].

5.2 Hemolytic Anemia

Cases of hemolytic anemia in patients treated with hydroxyurea for myeloproliferative diseases have been reported [see Adverse Reactions (6.1)]. Patients who develop acute jaundice or hematuria in the presence of persistent or worsening of anemia should have laboratory tests evaluated for hemolysis (e.g., measurement of serum lactate dehydrogenase, haptoglobin, reticulocyte, unconjugated bilirubin levels, urinalysis, and direct and indirect antiglobulin [Coombs] tests). In the setting of confirmed diagnosis of hemolytic anemia and in the absence of other causes, discontinue XROMI.

5.3 Malignancies

Hydroxyurea is a human carcinogen. In patients receiving long-term hydroxyurea for myeloproliferative disorders (a condition for which XROMI is not approved), secondary leukemia has been reported.

Secondary leukemia has also been reported in patients treated with long-term hydroxyurea for sickle cell anemia. Leukemia has also been reported in patients with sickle cell anemia and no prior history of treatment with hydroxyurea.

All patients using XROMI should be followed up on a long-term basis with regular blood counts to detect development of leukemia.

Skin cancer has also been reported in patients receiving long-term hydroxyurea. Advise protection from sun exposure and monitor for the development of secondary malignancies.

5.4 Embryo-Fetal Toxicity with Unapproved Use in Adolescents and Adults

Based on the mechanism of action and findings in animals, XROMI can cause fetal harm when administered to a pregnant woman. Hydroxyurea was embryotoxic and teratogenic in rats and rabbits at doses 0.8 times and 0.3 times, respectively, the maximum recommended human daily dose on a mg/m^2 basis.

5.5 Vasculitic Toxicities

Cutaneous vasculitic toxicities, including vasculitic ulcerations and gangrene, have occurred in patients with myeloproliferative disorders during therapy with hydroxyurea. These vasculitic toxicities were reported most often in patients with a history of, or currently receiving, interferon therapy. If cutaneous vasculitic ulcers occur, institute treatment and discontinue XROMI.

5.6 Live Vaccinations

Avoid use of live vaccines in patients taking XROMI. Concomitant use of XROMI with a live virus vaccine may potentiate the replication of the virus and/or may increase the adverse reaction of the vaccine because normal defense mechanisms may be suppressed by XROMI. Vaccination with live vaccines in a patient receiving XROMI may result in severe infection [see Drug Interactions (7.2)]. Patient’s antibody response to vaccines may be decreased. Consider consultation with a specialist.

5.7 Risks with Concomitant Use of Antiretroviral Drugs

Pancreatitis, hepatotoxicity, and peripheral neuropathy have occurred when hydroxyurea was administered concomitantly with antiretroviral drugs, including didanosine and stavudine [see Drug Interactions (7.1)].

5.8 Macrocytosis

XROMI may cause macrocytosis, which is self-limiting, and is often seen early in the course of treatment. The morphologic change resembles pernicious anemia, but is not related to vitamin B12 or folic acid deficiency. This may mask the diagnosis of pernicious anemia. Prophylactic administration of folic acid is recommended.

5.9 Pulmonary Toxicity

Interstitial lung disease including pulmonary fibrosis, lung infiltration, pneumonitis, and alveolitis/allergic alveolitis (including fatal cases) have been reported in patients treated for myeloproliferative neoplasm. Safety and effectiveness have not been established for the use of XROMI in the treatment of myeloproliferative neoplasms and the use is not approved by the FDA. Monitor patients developing pyrexia, cough, dyspnea, or other respiratory symptoms frequently, investigate and treat promptly. Discontinue XROMI and manage with corticosteroids [see Adverse Reactions (6.1)].

5.10 Laboratory Test Interference

Interference with uric acid, urea, or lactic acid assays is possible, rendering falsely elevated results of these in patients treated with hydroxyurea [see Drug Interactions (7.2)].

Hydroxyurea may falsely elevate sensor glucose results from certain continuous glucose monitoring (CGM) systems and may lead to hypoglycemia if sensor glucose results are relied upon to dose insulin.

If a patient using a CGM is to be prescribed hydroxyurea, consult with the CGM prescriber about alternative glucose monitoring methods [see Drug Interactions (7.2)].

6 ADVERSE REACTIONS

The following clinically significant adverse reactions are described in detail in other labeling sections:

- Myelosuppression [see Warnings and Precautions (5.1)]
- Hemolytic anemia [see Warnings and Precautions (5.2)]
- Malignancies [see Warnings and Precautions (5.3)]
- Vasculitic toxicities [see Warnings and Precautions (5.5)]
- Live vaccinations [see Warnings and Precautions (5.6)
- Risks with concomitant use of antiretroviral drugs [see Warnings and Precautions (5.7)]
- Macrocytosis [see Warnings and Precautions (5.8)]
- Pulmonary toxicity[see Warnings and Precautions (5.9)]

6.1 Clinical Trials Experience

Because clinical trials are conducted under widely varying conditions, adverse reaction rates observed in the clinical trials of a drug cannot be directly compared to rates in the clinical trials of another drug and may not reflect the rates observed in practice.

The safety of XROMI was evaluated in 32 pediatric patients aged 10 months -16 years with sickle cell anemia in a single-arm, open-label, prospective, multi-center, pharmacokinetic, safety and efficacy study (HUPK study). Only adverse reactions associated with the use of XROMI in pediatric patients aged 10 months to less than 2 years are presented.

The most frequently reported adverse reactions in HUPK study (<33%) were neutropenia, and thrombocytopenia [see Table 3].

Table 3. Adverse Reactions Reported in Pediatric Patients Aged 10 Months and Older Enrolled in HUPK
 | 10 Months–<2 Years | 2 –<6 Years | 6 –<18 Years | Overall
Body System Adverse Reactions | (n=6)% | (n=16)% | (n=10)% | (n=32)%
Neutropenia | 3 (50) | 1 (6) | 0 | 4 (13)
Thrombocytopenia | 2 (33) | 1 (6) | 0 | 3 (9)
Diarrhea | 1 (17) | 0 | 0 | 1 (3)
GGT Increased | 0 | 0 | 1(10) | 1 (3)
Absolute Reticulocyte Count Decreased | 1 (17) | 0 | 0 | 1 (3)
Alopecia | 0 | 1 (6) | 0 | 1 (3)
Nail Discolouration | 0 | 0 | 1 (10) | 1 (3)
Rash | 0 | 0 | 1 (10) | 1 (3)
Rash Popular | 0 | 1 (6) | 1 (10) | 2 (6)

6.2 Post marketing Experience

The following adverse reactions have been identified during post-approval use of hydroxyurea. Because these reactions are reported voluntarily from a population of uncertain size, it is not always possible to reliably estimate their frequency.

- Reproductive System and Breast disorders: azoospermia, and oligospermia
- Gastrointestinal disorders: stomatitis, nausea, vomiting, diarrhea, and constipation
- Metabolism and Nutrition disorders: anorexia
- Skin and subcutaneous tissue disorders: maculopapular rash, skin ulceration, cutaneous lupus erythematosus, dermatomyositis-like skin changes, peripheral and facial erythema, hyperpigmentation, nail hyperpigmentation, atrophy of skin and nails, scaling, violet papules, and alopecia
- Renal and urinary disorders: dysuria, elevations in serum uric acid, blood urea nitrogen (BUN), and creatinine levels
- Nervous system disorders: headache, dizziness, drowsiness, disorientation, hallucinations, and convulsions
- General disorders: fever, chills, malaise, edema, and asthenia
- Hepatobiliary disorders: elevation of hepatic enzymes, cholestasis, and hepatitis
- Respiratory disorders: diffuse pulmonary infiltrates, dyspnea, and pulmonary fibrosis, interstitial lung disease, pneumonitis, alveolitis, allergic alveolitis and cough
- Immune disorders: systemic lupus erythematosus
- Hypersensitivity: Drug-induced fever (pyrexia) (>39°C, >102°F) requiring hospitalization has been reported concurrently with gastrointestinal, pulmonary, musculoskeletal, hepatobiliary, dermatological or cardiovascular manifestations. Onset typically occurred within 6 weeks of initiation and resolved upon discontinuation of hydroxyurea. Upon re-administration fever reoccurred typically within 24 hours.
- Blood and lymphatic system disorders: hemolytic anemia

7 DRUG INTERACTIONS

7.1 Increased Toxicity with Concomitant Use of Antiretroviral Drugs

Pancreatitis
In patients with HIV infection during therapy with hydroxyurea and didanosine, with or without stavudine, fatal and nonfatal cases of pancreatitis have occurred. Hydroxyurea is not indicated for the treatment of HIV infection; however, if patients with HIV infection are treated with hydroxyurea, and in particular, in combination with didanosine and/or stavudine, close monitoring for signs and symptoms of pancreatitis is recommended. Permanently discontinue therapy with hydroxyurea in patients who develop signs and symptoms of pancreatitis.

Hepatotoxicity
Hepatotoxicity and hepatic failure resulting in death have been reported during postmarketing surveillance in patients with HIV infection treated with hydroxyurea and other antiretroviral drugs. Fatal hepatic events were reported most often in patients treated with the combination of hydroxyurea, didanosine, and stavudine. Avoid this combination.

Peripheral Neuropathy
Peripheral neuropathy, which was severe in some cases, has been reported in patients with HIV infection receiving hydroxyurea in combination with antiretroviral drugs, including didanosine, with or without stavudine.

7.2 Laboratory Test Interference

Interference with Uric Acid, Urea, or Lactic Acid Assays

Studies have shown that there is an analytical interference of hydroxyurea with the enzymes (urease, uricase, and lactate dehydrogenase) used in the determination of urea, uric acid, and lactic acid, rendering falsely elevated results of these in patients treated with hydroxyurea.

Interference with Continuous Glucose Monitoring Systems
Hydroxyurea may falsely elevate sensor glucose results from certain continuous glucose monitoring (CGM) systems and may lead to hypoglycemia if sensor glucose results are relied upon to dose insulin.

If a patient using a CGM is to be prescribed hydroxyurea, consult with the CGM prescriber about alternative glucose monitoring methods.

8 USE IN SPECIFIC POPULATIONS

8.1 Pregnancy

Risk Summary
XROMI can cause fetal harm based on findings from animal studies and the drug’s mechanism of action [see Clinical Pharmacology (12.1)]. There are no data with XROMI use in pregnant women to inform a drug-associated risk. In animal reproduction studies, administration of hydroxyurea to pregnant rats and rabbits during organogenesis produced embryotoxic and teratogenic effects at doses 0.8 times and 0.3 times, respectively, the maximum recommended human daily dose on a mg/m^2 basis (see Data). Advise women of the potential risk to a fetus and to avoid becoming pregnant while being treated with XROMI.
In the U.S. general population, the estimated background risk of major birth defects and miscarriage in clinically recognized pregnancies is 2%–4% and 15%–20%, respectively.

Data
Animal Data
Hydroxyurea has been demonstrated to be a potent teratogen in a wide variety of animal models, including mice, hamsters, cats, miniature swine, dogs, and monkeys at doses within 1-fold of the human dose given on a mg/m^2 basis. Hydroxyurea is embryotoxic and causes fetal malformations (partially ossified cranial bones, absence of eye sockets, hydrocephaly, bipartite sternebrae, missing lumbar vertebrae) at 180 mg/kg/day (about 0.8 times the maximum recommended human daily dose on a mg/m^2 basis) in rats and at 30 mg/kg/day (about 0.3 times the maximum recommended human daily dose on a mg/m^2 basis) in rabbits. Embryotoxicity was characterized by decreased fetal viability, reduced live litter sizes, and developmental delays. Hydroxyurea crosses the placenta. Single doses of ≥375 mg/kg (about 1.7 times the maximum recommended human daily dose on a mg/m^2 basis) to rats caused growth retardation and impaired learning ability.

8.2 Lactation

Risk Summary
It is not known whether XROMI is excreted in human milk, the effects of XROMI on the breastfed child, or the effects of XROMI on milk production. Because of the potential for serious adverse reactions in a breastfed child from XROMI, including carcinogenicity, advise patients not to breastfeed during treatment with XROMI.

8.3 Females and Males of Reproductive Potential

Pregnancy Testing
Verify the pregnancy status of females of reproductive potential prior to initiating XROMI therapy.
Contraception
Females
XROMI can cause fetal harm when administered to a pregnant woman [see Use in Specific Populations (8.1)]. Advise females of reproductive potential to use effective contraception during and after treatment with XROMI for at least 6 months after therapy. Advise females to immediately report pregnancy.
Males
XROMI may damage spermatozoa and testicular tissue, resulting in possible genetic abnormalities. Males with female sexual partners of reproductive potential should use effective contraception during and after treatment with XROMI for at least 1 year after therapy [see Nonclinical Toxicology (13.1)].
Infertility
Males
Based on findings in animals and humans, male fertility may be compromised by treatment with XROMI. Azoospermia or oligospermia, sometimes reversible, has been observed in men. Inform male patients about the possibility of sperm conservation before the start of therapy [see Nonclinical Toxicology (13.1)].

8.4 Pediatric Use

The safety and effectiveness of XROMI have been established in pediatric patients aged 6 months and older with sickle cell anemia with recurrent moderate to severe painful crises. Use of XROMI in these age groups is supported by evidence from a pharmacokinetic, efficacy and safety study, in which 32 pediatric patients ages 6 months to <18 years were enrolled. Among the 32 pediatric patients treated with XROMI, 6 were infants (6 months – 2 years), 16 children (2-6 years) and 10 were adolescents (6-18 years) [see Clinical Studies (14)].
Continuous follow-up of the growth of treated children is recommended.

8.6 Renal Impairment

The exposure to XROMI is higher in patients with creatinine clearance of less than 60 mL/min. Reduce dosage and closely monitor the hematologic parameters when XROMI is to be administered to these patients [see Dosage and Administration (2.2) and Clinical Pharmacology (12.3)].

8.7 Hepatic Impairment

There are no data that support specific guidance for dosage adjustment in patients with hepatic impairment. Close monitoring of hematologic parameters is advised in these patients.

10 OVERDOSAGE

Acute mucocutaneous toxicity and neutropenia has been reported in patients receiving hydroxyurea at doses several times above the therapeutic dose. Soreness, violet erythema, oedema on palms and soles followed by scaling of hand and feet, severe generalized hyperpigmentation of the skin and stomatitis have been observed.

11 DESCRIPTION

XROMI (hydroxyurea) is available for oral use as oral solution containing 100 mg/mL hydroxyurea. Inactive ingredients include methyl parahydroxybenzoate, purified water, sodium hydroxide, strawberry flavor, sucralose and xanthan gum.
Hydroxyurea is a white to off-white crystalline powder. It is hygroscopic and freely soluble in water, but practically insoluble in alcohol. The empirical formula is CH4N2O2 and it has a molecular weight of 76.05. Its structural formula is:

12 CLINICAL PHARMACOLOGY

12.1 Mechanism of Action

The precise mechanism by which hydroxyurea produces its cytotoxic and cytoreductive effects is not known. However, various studies support the hypothesis that hydroxyurea causes an immediate inhibition of DNA synthesis by acting as a ribonucleotide reductase inhibitor, without interfering with the synthesis of ribonucleic acid or of protein.
The mechanisms by which XROMI produces its beneficial effects in patients with sickle cell anemia are uncertain. Known pharmacologic effects of XROMI that may contribute to its beneficial effects include increasing HbF levels in red blood cells (RBCs), decreasing neutrophils, increasing the water content of RBCs, increasing deformability of sickled cells, and altering the adhesion of RBCs to endothelium.

12.2 Pharmacodynamics

In pediatric patients treated with hydroxyurea for up to 15 months, the ratio of fetal hemoglobin to total hemoglobin was 25%, 23.6% and 11.2% at the end of the study, representing a change from baseline increase of 9%, 148% and 167% in patients aged 6 months to <2 years, 2 to <6 years and 6 to <18 years, respectively.

12.3 Pharmacokinetics

Absorption
Following oral administration of XROMI, hydroxyurea reaches peak plasma concentrations in 0 to 2 hours. Mean peak plasma concentrations and AUCs increase more than proportionally with increase of dose.

Effect of Food
There are no data on the effect of food on the absorption of hydroxyurea.

Distribution
Hydroxyurea distributes throughout the body with a volume of distribution approximating total body water. Hydroxyurea concentrates in leukocytes and erythrocytes.

Elimination
Metabolism
Up to 60% of an oral dose undergoes conversion through saturable hepatic metabolism and a minor pathway of degradation by urease found in intestinal bacteria.

Excretion
In patients with sickle cell anemia, the mean cumulative urinary recovery of hydroxyurea was about 40% of the administered dose.

Specific Populations
Renal Impairment
The effect of renal impairment on the pharmacokinetics of hydroxyurea was assessed in adult patients with sickle cell anemia and renal impairment. Patients with normal renal function (creatinine clearance [CrCl] >80 mL/min), mild (CrCl 50-80 mL/min), moderate (CrCl =30-<50 mL/min), or severe (<30 mL/min) renal impairment received a single oral dose of 15 mg/kg hydroxyurea. Creatinine clearance values were obtained using 24-hour urine collections. Patients with ESRD received two doses of 15 mg/kg separated by 7 days; the first was given following a 4-hour hemodialysis session, the second prior to hemodialysis. The exposure to hydroxyurea (mean AUC) in patients with CrCl <60 mL/min and those with ESRD was 64% higher than in patients with normal renal function (CrCl >60 mL/min). [see Dosage and Administration (2.2) and Use in Specific Populations (8.6)].

Pediatric Patients
The model estimated steady state exposures (AUC) in pediatric patients receiving a daily dose of 15 mg/kg is lower in patients aged 6 months to <2 years and 2 to <6 years by 40% and 28% compared to adults receiving the same dose while the exposures in 6 to <18 year old patients are similar to adult exposures (XROMI is not approved for use in adults).

13 NONCLINICAL TOXICOLOGY

13.1 Carcinogenesis, Mutagenesis, Impairment of Fertility

Conventional long-term studies to evaluate the carcinogenic potential of hydroxyurea have not been performed. However, intraperitoneal administration of 125 to 250 mg/kg hydroxyurea (about 0.6-1.2 times the maximum recommended human oral daily dose on a mg/m^2 basis) thrice weekly for 6 months to female rats increased the incidence of mammary tumors in rats surviving to 18 months compared to control. Hydroxyurea is mutagenic in vitro to bacteria, fungi, protozoa, and mammalian cells. Hydroxyurea is clastogenic in vitro (hamster cells, human lymphoblasts) and in vivo (SCE assay in rodents, mouse micronucleus assay). Hydroxyurea causes the transformation of rodent embryo cells to a tumorigenic phenotype [see Warnings and Precautions (5.3 , 5.4)].
Hydroxyurea administered to male rats at 60 mg/kg /day (about 0.3 times the maximum recommended human daily dose on a mg/m^2 basis) produced testicular atrophy, decreased spermatogenesis and significantly reduced their ability to impregnate females [see Use in Specific Populations (8.3)].

14 CLINICAL STUDIES

The effectiveness of XROMI has been established for the indication, “to reduce the frequency of painful crises and to reduce the need for blood transfusions in pediatric patients aged 6 months and older with sickle cell anemia with recurrent moderate to severe painful crises” based on an adequate and well-controlled study of hydroxyurea capsules in adult patients with sickle cell anemia with recurrent moderate to severe pain crises and additional pharmacokinetic data from a single-arm, open-label study of XROMI in pediatric patients aged 10 months to less than 18 years with sickle cell anemia, who were treatment naïve or had not received hydroxyurea in the 6 months prior to enrollment: HUPK study [see Adverse Reactions (6.1)].

15 REFERENCES

OSHA Hazardous Drugs. OSHA. http://www.osha.gov/SLTC/hazardousdrugs/index.html

16 HOW SUPPLIED/STORAGE AND HANDLING

16.1 How Supplied

XROMI (hydroxyurea) 100 mg/mL is a colorless to pale yellow liquid supplied in an Amber type III glass bottle with tamper evident child-resistant closure (HDPE with expanded polyethylene liner) containing 148 mL of oral solution.
Each carton NDC 62484-0015-5 contains 1 bottle XROMI NDC 62484-0015-4, an LDPE bottle adaptor and 2 oral dosing syringes (one oral dosing syringe graduated to 3 mL and one oral dosing syringe graduated to 10 mL).

16.2 Storage

Store XROMI between 2°C to 8°C (35°F to 46°F) excursions permitted to 25°C (77°F) for up to 72 hours. Keep the bottle tightly closed to protect the integrity of the product and minimize the risk of accidental spillage. Do not freeze.
Use within 12 weeks after initially opening the bottle. Discard unused XROMI remaining after 12 weeks of first opening the bottle.

16.3 Handling and Disposal

XROMI is a hazardous drug. Follow applicable special handling and disposal procedures [see References (15)].
Anyone handling XROMI should wash their hands before and after administering a dose. To decrease the risk of exposure, parents and caregivers should wear disposable gloves when handling XROMI. To minimize air bubbles, the bottle should not be shaken prior to dosing. XROMI contact with skin or mucous membrane must be avoided. If XROMI comes into contact with skin or mucosa, it should be washed immediately and thoroughly with soap and water. Spillages must be wiped immediately with a damp disposable towel and discarded in a closed container, such as a plastic bag. The spill areas should be cleaned three times using a detergent solution followed by clean water. If contact with XROMI occurs in the eye(s), flush the eye(s) thoroughly with water or isotonic eyewash designated for that purpose for at least 15 minutes. Parents / care givers should be advised to keep hydroxyurea out of the sight and reach of children. Accidental ingestion can be lethal for children.
Oral dosing syringes should be rinsed and washed with cold or warm water and dried completely before the next use. Store oral dosing syringes in a hygienic place with the medicine.

17 PATIENT COUNSELING INFORMATION

Advise the caregiver to read the FDA-approved patient labeling (Instructions for Use and Medication Guide).

- There is a risk of myelosuppression. Emphasize the importance of monitoring blood counts every two weeks throughout the duration of therapy to caregivers of patients taking XROMI [see Warnings and Precautions (5.1)]. Advise caregivers to report signs and symptoms of infection or bleeding in patients immediately.
- Advise caregivers of the risk of hemolytic anemia. Advise caregivers that the patient will have blood tests to evaluate for this if they develop persistent anemia. [see Warnings and Precautions (5.2)].
- Advise caregivers that there is a risk of cutaneous vasculitic toxicities and secondary malignancies including leukemia. Advise use of sun protection [see Warnings and Precautions (5.3,5.5)].
- Advise caregivers to inform the patient's healthcare provider if they have received or are planning to receive vaccinations while taking XROMI as this may result in a severe infection [see Warnings and Precautions (5.6)].
- Advise females of reproductive potential of the potential risk to a fetus should they become pregnant while taking XROMI. Advise patients to inform their healthcare provider of a known or suspected pregnancy. Advise females and males of reproductive potential to use contraception during and after treatment with XROMI [see Warnings and Precautions (5.4) and Use in Specific Populations (8.1,8.3)].
- Advise females to discontinue breastfeeding during treatment with XROMI [see Use in Specific Populations (8.2)].
- Advise male patients of potential risk to fertility.
- Advise caregivers of patients with HIV infection to contact their healthcare provider for signs and symptoms of pancreatitis, hepatic events, and peripheral neuropathy [see Warnings and Precautions (5.7)].
- Advise patients to notify their healthcare provider if they are using a continuous glucose monitoring system while taking XROMI [see Warnings and Precautions (5.9)]. Advise caregivers of the symptoms of potential pulmonary toxicity and instruct them to seek prompt medical attention for the patient in the event of pyrexia, cough, dyspnea, or other respiratory symptoms [see Warnings and Precautions (5.9)].

Because XROMI package includes two oral dosing syringes, advise patients on which oral dosing syringe they should use.

Manufactured by:
Nova Laboratories Ltd.
Leicester
LE18 4YL
United Kingdom

Manufactured for:
Rare Disease Therapeutics, Inc.
2550 Meridian Blvd., Suite 150
Franklin, Tennessee 37067
www.raretx.com

U.S. Patent: 12,409,156

Part Number: D001506/1

PATIENT INFORMATION

MEDICATION GUIDE
XROMI® (ex-ro-mee)
(hydroxyurea)
oral solution

What is the most important information I should know about XROMI?

XROMI can cause serious side effects including:

- Low blood cell counts are common with XROMI, including low red blood cells, white blood cells, and platelets, and can be severe and life-threatening. If your child's white blood cell count becomes very low, your child is at increased risk for infection. Your child's healthcare provider will check your child's blood cell counts before and during treatment with XROMI. Your child's healthcare provider may change your child's dose or tell your child to stop taking XROMI if your child has low blood cell counts. Tell your child's healthcare provider right away if your child gets any of the following symptoms:

- fever or chills
- body aches
- feeling very tired

- shortness of breath
- bleeding or unexplained bruising

- Hemolytic Anemia, the fast breakdown of red blood cells, has happened in people who take XROMI. Tell your child’s healthcare provider if your child develops yellowing of their skin (jaundice) or blood in their urine. Your child’s healthcare provider may do blood tests if your child has persistent or worsening anemia not related to sickle cell anemia.
- Cancer. Some people have developed cancer, such as leukemia and skin cancer, after taking XROMI for a long time. Your child's healthcare provider will check your child for cancer. You should protect your child's skin from the sun using sunblock, hats, and sun-protective clothing.
- XROMI can harm an unborn baby.
  Females taking XROMI who can become pregnant should:
  • avoid becoming pregnant during treatment with XROMI.
  • talk with your healthcare provider about the risks of XROMI to your unborn baby.
  • use effective birth control during treatment with XROMI and for at least 6 months after treatment.
  • expect that their healthcare provider will perform a pregnancy test before they start treatment with XROMI.
  • tell their healthcare provider right away if you become pregnant or think you may be pregnant.
  For males taking XROMI:
  If your child has a female sexual partner who can become pregnant, your child should use effective birth control during treatment with XROMI and for at least 6 months after treatment.

XROMI may cause fertility problems in males. Talk to your child’s healthcare provider if this is a concern for you.

What is XROMI?
XROMI is a prescription medicine that is used to reduce the frequency of painful crises and reduce the need for blood transfusions in children aged 6 months of age and older with sickle cell anemia with recurrent moderate to severe painful crises.
XROMI is not for use in adults.
It is not known if XROMI is safe and effective in children less than 6 months old.

Your child should not take XROMI if your child is allergic to hydroxyurea or any of the ingredients in XROMI. See the end of this Medication Guide for a list of the ingredients in XROMI.

Before taking XROMI, tell your healthcare provider about all of your medical conditions, including if you:

- have kidney problems or is receiving hemodialysis.
- have liver problems.
- have human immunodeficiency virus (HIV) or take HIV medicines. Taking XROMI with certain HIV medicines can cause serious reactions and may lead to death. Tell your child's healthcare provider if your child takes an HIV medicine.
- have increased levels of uric acid in their blood (hyperuricemia).
- have a history of receiving interferon therapy or is currently receiving interferon therapy.
- have leg wounds or ulcers.
- plan to receive any vaccinations. You should not receive "live vaccines" during treatment with XROMI.
- are pregnant or plan to become pregnant. See “What is the most important information I should know about XROMI?”
- are breastfeeding or plan to breastfeed. It is not known if XROMI can pass into your breast milk. Do not breastfeed during treatment with XROMI.
- are using a continuous glucose monitor (CGM) to test your blood glucose. Hydroxyurea may affect your sensor glucose results and may lead to low blood sugar (hypoglycemia). Talk to the healthcare provider that prescribed your CGM about whether it is safe to use while you are taking XROMI.

Tell your healthcare provider about all the medicines your child takes, including prescription and over-the-counter medicines, vitamins, and herbal supplements.

How should your child take XROMI?

Read the Instructions for Use that comes with XROMI for information about the right way to measure and give a dose of XROMI. If you have any questions, talk to your child's healthcare provider or pharmacist.

- Administer XROMI exactly as your child's healthcare provider tells you to administer it. XROMI is taken 1 time a day at the same time each day.
- Administer XROMI with or after meals. Administer XROMI the same way each day.
- Drink some water after each dose of XROMI.
- If your child takes too much XROMI, call your child's healthcare provider or go to the nearest hospital emergency room.
- If you miss a dose of XROMI, call your healthcare provider for advice.
- XROMI oral solution should be handled with care. To decrease the risk of exposure, caregivers should do the following when handling XROMI:
- Wear disposable gloves when handling oral dosing syringes or bottles containing XROMI.
- Wash your hands with soap and water before and after handling oral dosing syringes or bottles containing XROMI.
- Avoid contact with the oral solution. If contact with the oral solution happens on the skin, wash the skin area right away and thoroughly with soap and water. If contact with the oral solution happens in the eyes, flush the eyes thoroughly with water and isotonic eyewash used for that purpose for at least 15 minutes.
- If the oral solution is spilled, wipe it up right away with a damp disposable towel. Throw the damp disposable towel away in a closed container such as a plastic bag. The spill area should then be cleaned up using a detergent solution followed by clean water.
- During treatment with XROMI, your child's healthcare provider will do blood tests regularly to check your child's blood cell counts and liver function. Your healthcare provider may change your child's dose if your child has side effects.

What are the possible side effects of XROMI?
XROMI may cause serious side effects, including:
See What is the most important information I should know about XROMI?"

- Skin ulcers and death of tissue (gangrene) have happened in people who take XROMI. This has happened most often in people who receive interferon therapy or have a history of interferon therapy. Your child's healthcare provider will decrease your dose or stop treatment with XROMI if your child develops any skin ulcers.
- Enlarged red blood cells (macrocytosis). Macrocytosis is common in people who take XROMI and can make it difficult to detect a decrease of folic acid. Your child's healthcare provider may prescribe a folic acid supplement for your child.
- Respiratory (breathing) problems. Some people have developed life-threatening respiratory conditions called interstitial lung disease. Your child’s healthcare provider may tell your child to stop taking XROMI if your child develops respiratory problems. Tell your child’s healthcare provider right away if your child gets any of the following symptoms:
  • fever
  • cough
  • shortness of breath

The most common side effects of XROMI include:

- low blood levels of a type of white blood cell (neutropenia)
- low blood levels of platelets (thrombocytopenia)
- raised bumps on the skin (papular rash)

These are not all the possible side effects of XROMI.
Call your child's doctor for medical advice about side effects. You may report side effects to FDA at 1-800-FDA-1088.

How should I store XROMI?

- XROMI comes in a bottle with a child-resistant cap.
- Refrigerate XROMI between 35°F to 46°F (2°C to 8°C). Do not freeze.
- Store the XROMI bottle and oral dosing syringe in a clean place.
- XROMI oral solution should be used within 12 weeks after opening the bottle. Dispose of (throw away) any unused medicine and the dosing syringes after 12 weeks.
- Do not use after the expiration date on the carton and bottle.

Keep XROMI and all medicines out of the reach of children.

General information about the safe and effective use of XROMI
Medicines are sometimes prescribed for purposes other than those listed in a Medication Guide. Do not use XROMI for a condition for which it was not prescribed. Do not give XROMI to other people, even if they have the same symptoms your child has. It may harm them. You can ask your child's healthcare provider or pharmacist for information about XROMI that is written for health professionals.

What are the ingredients of XROMI?
Active ingredient: hydroxyurea
Inactive ingredients: methyl parahydroxybenzoate, purified water, sodium hydroxide, strawberry flavor, sucralose and xanthan gum.

Manufactured by: Nova Laboratories Ltd., Leicester, LE18 4YL, United Kingdom
Manufactured for: Rare Disease Therapeutics, Inc., 2550 Meridian Blvd., Suite 150, Franklin, TN 37067
For more information, go to www.xromi-us.com.
Part Number: D001230/1

This Medication Guide has been approved by the U.S. Food and Drug Administration.

Issued: DEC 2024

INSTRUCTIONS FOR USE
XROMI®(ex-ro-mee)
hydroxyurea)
oral solution

Read these Instructions for Use before your child starts taking XROMI, and each time you get a refill. There may be new information. This Instructions for Use does not take the place of talking to your child's healthcare provider about your child's medical condition or treatment.

Important information:

- Always use the oral dosing syringe provided with your child's XROMI oral solution to measure your child's prescribed dose. Ask your child’s healthcare provider or pharmacist to show you which oral dosing syringe to use and how to measure your child’s prescribed dose if you are not sure.
- Wash your hands with soap and water before and after handling XROMI oral solution and oral dosing syringes.
- Wear disposable gloves when handling XROMI oral solution and oral dosing syringes.
- Avoid contact with the oral solution. If contact with the oral solution happens on the skin, nose, or mouth, wash the area right away and thoroughly with soap and water. If contact with the oral solution happens in the eyes, flush the eyes thoroughly with water and isotonic eyewash used for that purpose for at least 15 minutes.
- If the oral solution is spilled, wipe it up right away with a damp disposable towel. Throw the damp disposable towel away in a closed container such as a plastic bag. The spill area should then be cleaned up using a detergent solution followed by clean water.
- Do not shake the bottle.
  Each carton of XROMI oral solution contains:
  • 1 bottle of XROMI oral solution
  • 1 bottle adapter
  • One 3 mL oral dosing syringe (for doses of 3 mL or less)
  • One 10 mL oral dosing syringe (for doses more than 3 mL)

If your carton does not contain two oral dosing syringes, contact your pharmacist.
You will also need disposable gloves.

Before giving XROMI:

Step 1. Wash your hands well with soap and water.

Step 2. Put on disposable gloves.

Step 3. Place the items from the carton on a clean flat surface.

Step 4. Open the bottle by pushing down firmly on the child-resistant cap and turning it counter-clockwise (See Figure A).
Do not throw away the child-resistant cap.

Figure A

Step 5. First time use only: Insert the bottle adapter.
Push the ribbed end of the bottle adapter into the neck of the bottle until it is firmly in place. The bottom edge of the adapter should fully contact the top rim of the bottle (See Figure B).
Do not remove the adapter from the bottle after it is inserted.

Figure B

Measuring your child's prescribed dose of XROMI:

Step 6. Choose the oral dosing syringe you need to measure your child's prescribed dose. (See Figure C).
Check the dose in mL as prescribed by your child’s healthcare provider. Choose the right oral dosing syringe for your child’s dose.

- Use the 3 mL oral dosing syringe for doses of 3 mL or less.
- Use the 10 mL oral dosing syringe for doses more than 3 mL.

Find the marking for your child’s prescribed dose on the right oral dosing syringe.

Figure C

Step 7. Push the plunger of the oral dosing syringe all the way down to remove any air in the oral dosing syringe (See Figure D).

Figure D

Step 8. Hold the bottle upright. Insert the tip of the oral dosing syringe into the opening of the bottle adapter until it is firmly in place (See Figure E).

Figure E

Step 9. Turn the bottle upside down with the oral dosing syringe in place. Pull back slowly on the plunger of the oral dosing syringe until the top of the plunger is even with the mL mark on the oral dosing syringe that corresponds to your child’s prescribed dose.
See Figure F for an example of a dose of 6 mL. Your dose may be different than the example shown.

Figure F

Step 10. Leave the oral dosing syringe in the bottle adapter and turn the bottle upright. Place the bottle onto a flat surface. Hold the oral dosing syringe by the barrel and carefully remove it from the adapter. Do not hold the oral dosing syringe by the plunger (See Figure G).

Figure G

Step 11. Hold the oral dosing syringe with the oral dosing syringe tip pointing up. Check that the correct dose was drawn up into the oral dosing syringe (See Figure H).
If there are large air bubbles in the oral dosing syringe (See Figure I) or if you have drawn up the wrong dose, re-insert the oral dosing syringe tip firmly into the bottle adapter while the bottle is in an upright position. Fully push in the plunger so the oral solution flows back into the bottle. Repeat Steps 8 and 9.

Figure H
Figure I

Giving the prescribed dose of XROMI:

Step 12. Place the tip of the oral dosing syringe in your child’s mouth and place the tip against the inside of your child’s cheek.
Gently push the plunger all the way down to give all the medicine in the oral dosing syringe and then remove the oral dosing syringe from your child’s mouth (See Figure J).
Make sure the child has time to swallow the medicine.
If your child’s prescribed dose is more than 10 mL, you will need to divide the dose. Follow the instructions given to you by your healthcare provider or pharmacist about how to divide the dose and repeat Steps 6 through 12.

Figure J

Step 13. Have your child drink some water to make sure no medicine is left in your child’s mouth.

Step 14. Close the bottle tightly by turning the child-resistant cap clockwise, leaving the bottle adapter in place.

Step 15. Wash your hands well with soap and water.
Rinse and wash the oral dosing syringes with cold or warm water and dry completely before next use. Hold the oral dosing syringe under water and move the plunger up and down several times to make sure the inside of the oral dosing syringe is clean. Let the oral dosing syringe dry completely before you use it again. Do not throw away the oral dosing syringe after use.

Storing XROMI

- Store XROMI in a refrigerator between 35°F to 46°F (2°C to 8°C). Do not freeze.
- Store the XROMI bottle and oral dosing syringe in a clean place.
- XROMI oral solution should be used within 12 weeks after opening the bottle. Dispose of (throw away) any unused medicine and the dosing syringes after 12 weeks.
- Do not use after the expiration date on the carton and the bottle.
- Keep XROMI and all medicines out of the reach of children.

Disposing of XROMI

- Ask your pharmacist for instructions on how to throw away (dispose of) XROMI that is expired or no longer needed.

Manufactured by: Nova Laboratories Ltd., Leicester, LE18 4YL, United Kingdom
Manufactured for: Rare Disease Therapeutics, Inc., 2550 Meridian Blvd., Suite 150, Franklin, TN 37067
Part Number: D001426/1
This “Instructions for Use” has been approved by the U.S. Food and Drug Administration Revised: 12/2024

PACKAGE LABEL

XROMI Carton Label

XROMI Bottle label